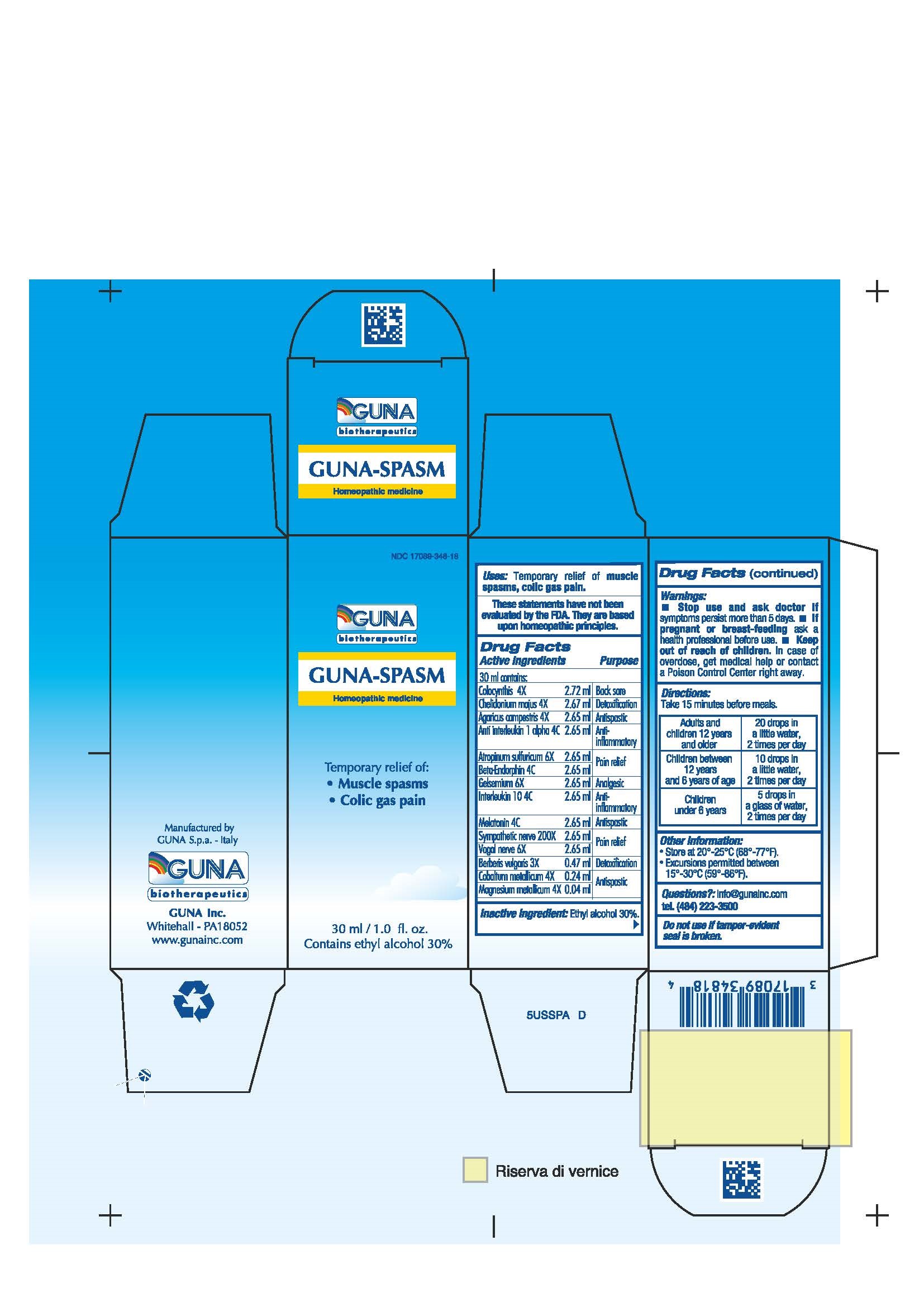 DRUG LABEL: GUNA-SPASM
NDC: 17089-348 | Form: SOLUTION/ DROPS
Manufacturer: Guna spa
Category: homeopathic | Type: HUMAN OTC DRUG LABEL
Date: 20181221

ACTIVE INGREDIENTS: CULTIVATED MUSHROOM 4 [hp_X]/30 mL; ANTI-INTERLEUKIN-1.ALPHA. IMMUNOGLOBULIN G RABBIT 4 [hp_C]/30 mL; ATROPINE SULFATE 6 [hp_X]/30 mL; BERBERIS VULGARIS ROOT BARK 3 [hp_X]/30 mL; METENKEFALIN 4 [hp_C]/30 mL; CHELIDONIUM MAJUS 4 [hp_X]/30 mL; COBALT 4 [hp_X]/30 mL; WATERMELON 4 [hp_X]/30 mL; GELSEMIUM SEMPERVIRENS ROOT 6 [hp_X]/30 mL; INTERLEUKIN-10 4 [hp_C]/30 mL; MAGNESIUM 4 [hp_X]/30 mL; MELATONIN 4 [hp_C]/30 mL; SUS SCROFA SYMPATHETIC NERVE 200 [hp_X]/30 mL; SUS SCROFA VAGUS NERVE 6 [hp_X]/30 mL
INACTIVE INGREDIENTS: ALCOHOL 9 mL/30 mL

GUNA-SPASM

ACTIVE INGREDIENTS/PURPOSE

AGARICUS CAMPESTRIS 4X ANTISPASTIC
ANTI INTERLEUKIN 1 ALPHA 4C ANTI-INFLAMMATORY
ATROPINUM SULFURICUM 6X PAIN RELIEF
BERBERIS VULGARIS 3X DETOXIFICATION
BETA-ENDORPHIN 4C PAIN RELIEF
CHELIDONIUM MAJUS 4X DETOXIFICATION
COBALTUM METALLICUM 4X ANTISPASTIC
COLOCYNTHIS 4X BACK SORE
GELSEMIUM 6X ANALGESIC
INTERLEUKIN 10 4C ANTI-INFLAMMATORY
MAGNESIUM METALLICUM 4X ANTISPASTIC
MELATONIN 4C ANTISPASTIC
SYMPATHETIC NERVE 200X PAIN RELIEF
VAGAL NERVE 6X PAIN RELIEF

USES

Temporary relief of:

- Muscle spasms
- Colic gas pain

WARNINGS

Stop use and ask doctor if symptoms persist more than 5 days.
If pregnant or breast-feeding ask a health professional before use.
Keep out of reach of children. In case of overdose, get medical help or contact a Poison Control Center right away.
Contains ethyl alcohol 30%

PREGNANCY

If pregnant or breast-feeding ask a doctor before use

WARNINGS

Keep this and all medicines out of reach of children

DIRECTIONS

Adults and children 12 years and older 20 drops in a little, 2 times per day
Children between 12 years and 6 years of age 10 drops in a little water, 2 times per day
Children under 6 years 5 drops in a glass of water, 2 times per day

QUESTIONS

Questions?: info@gunainc.com, tel. (484) 223-3500

INDICATIONS AND USAGE

Take 15 minutes before meals

Inactive Ingredient: Ethyl alcohol 30%.